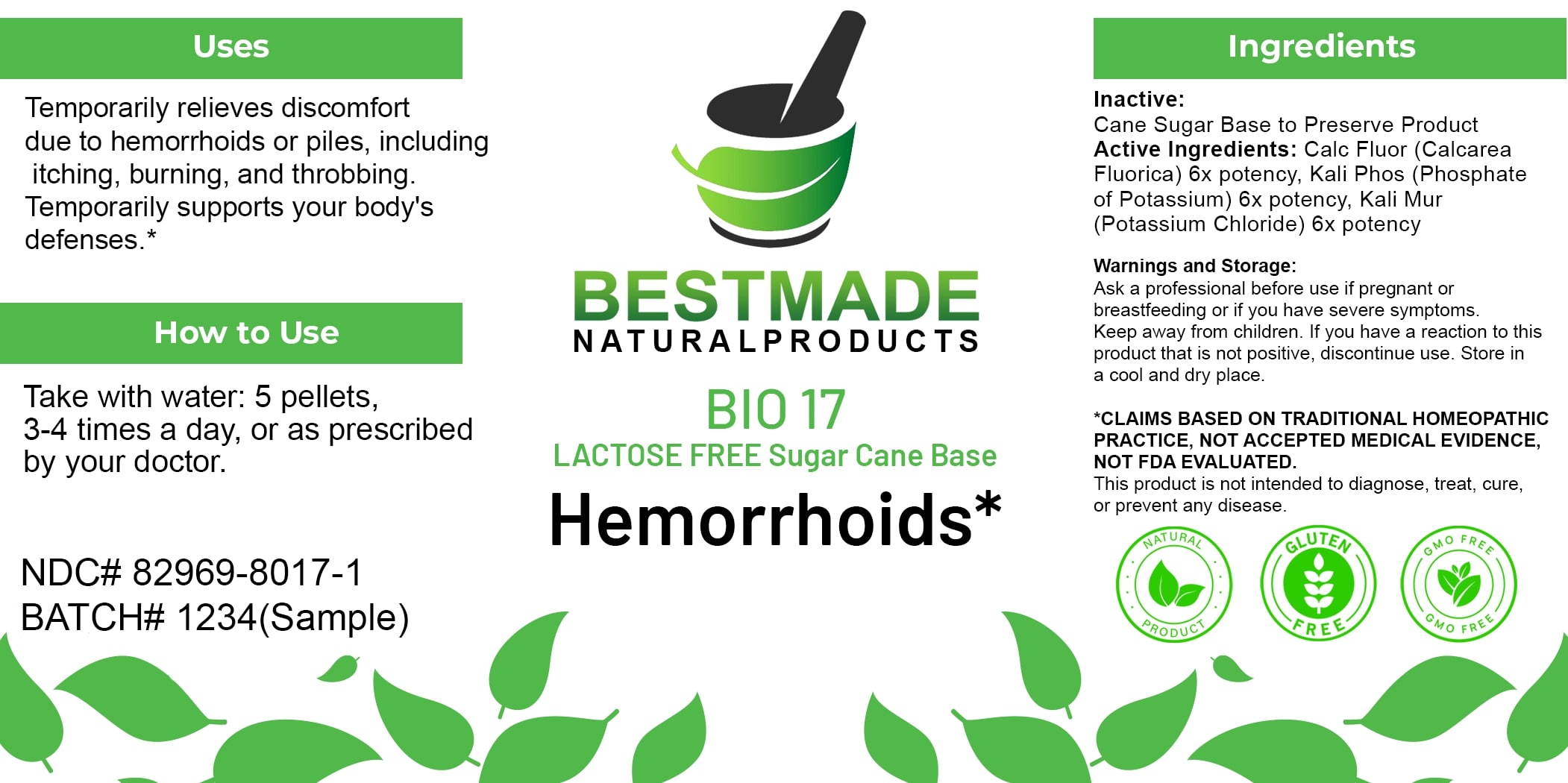 DRUG LABEL: Bestmade Natural Products BIO17 Lactose Free
NDC: 82969-8017 | Form: TABLET, SOLUBLE
Manufacturer: Bestmade Natural Products
Category: homeopathic | Type: HUMAN OTC DRUG LABEL
Date: 20250323

ACTIVE INGREDIENTS: DIBASIC POTASSIUM PHOSPHATE 6 [hp_X]/6 [hp_X]; CALCIUM FLUORIDE 6 [hp_X]/6 [hp_X]; POTASSIUM CHLORIDE 6 [hp_X]/6 [hp_X]
INACTIVE INGREDIENTS: SUCROSE 6 [hp_X]/6 [hp_X]

BIO17 Hemorrhoids* LACTOSE FREE Sugar Cane Base

DOSAGE AND ADMINISTRATION

How to Use

Take with water: 5 pellets, 3-4 times a day, or as prescribed by your doctor.

Inactive:

Cane Sugar Base to Preserve Product

Active Ingredients:

Calc Fluor (Calcarea Fluorica) 6x potency, Kali Phos (Phosphate of Potassium) 6x potency, Kali Mur (Potassium Chloride) 6x potency

Uses

Temporarily relieves discomfort due to hemorrhoids or piles, including itching, burning, and throbbing. Temporarily supports your body's defenses.*

*CLAIMS BASED ON TRADITIONAL HOMEOPATHIC PRACTICE, NOT ACCEPTED MEDICAL EVIDENCE, NOT FDA EVALUATED.

This product is not intended to diagnose, treat, cure, or prevent any disease.

Uses

Temporarily relieves discomfort due to hemorrhoids or piles, including itching, burning, and throbbing. Temporarily supports your body's defenses.*

*CLAIMS BASED ON TRADITIONAL HOMEOPATHIC PRACTICE, NOT ACCEPTED MEDICAL EVIDENCE, NOT FDA EVALUATED.

This product is not intended to diagnose, treat, cure, or prevent any disease.

KEEP OUT OF REACH OF CHILDREN

Warnings and Storage:

Ask a professional before use if pregnant or breastfeeding or if you have severe symptoms. Keep away from children. If you have a reaction to this product that is not positive, discontinue use. Store in a cool and dry place.

Warnings and Storage:

Ask a professional before use if pregnant or breastfeeding or if you have severe symptoms. Keep away from children. If you have a reaction to this product that is not positive, discontinue use. Store in a cool and dry place.

*CLAIMS BASED ON TRADITIONAL HOMEOPATHIC PRACTICE, NOT ACCEPTED MEDICAL EVIDENCE NOT FDA EVALUATED.

This product is not intended to diagnose, treat, cure, or prevent any disease.

Entire package label